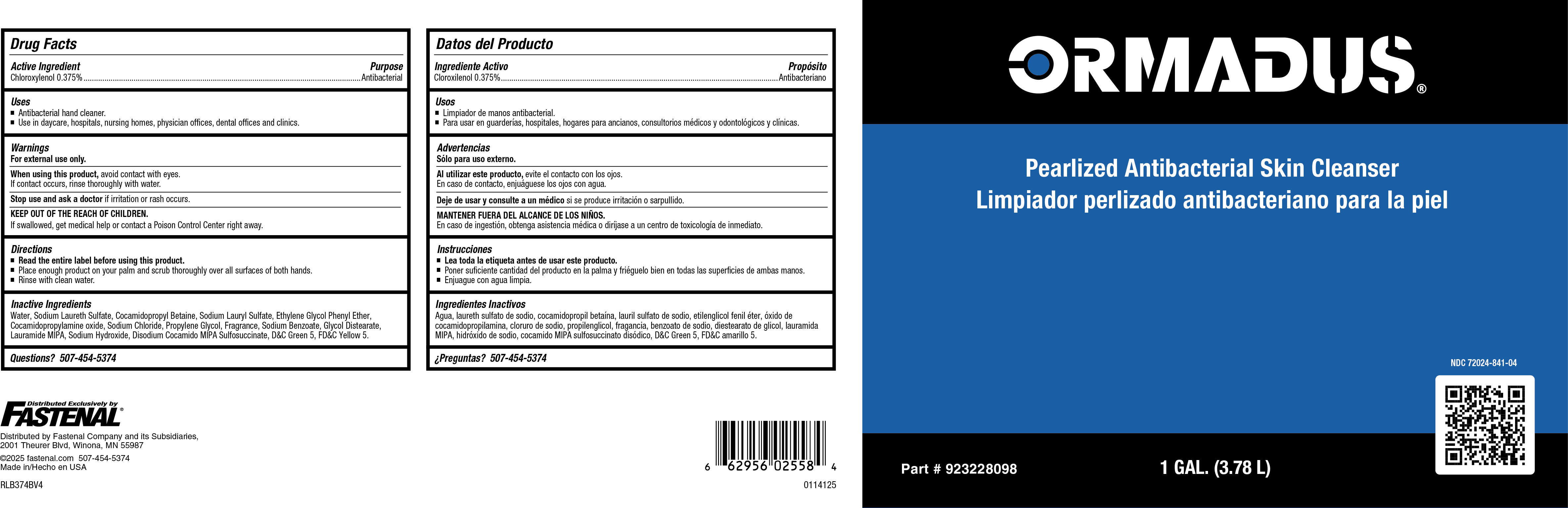 DRUG LABEL: Antibacterial Skin Cleanser
NDC: 72024-708 | Form: SOAP
Manufacturer: Fastenal
Category: otc | Type: HUMAN OTC DRUG LABEL
Date: 20251008

ACTIVE INGREDIENTS: CHLOROXYLENOL 4 mg/1 mL
INACTIVE INGREDIENTS: SODIUM CHLORIDE; ALCOHOL; D&C GREEN NO. 5; FD&C YELLOW NO. 5; MAGNESIUM NITRATE; DIMETHYL BENZYL CARBINYL BUTYRATE; ETHYL BUTYRATE; SODIUM FERROCYANIDE; ETHYL ACETOACETATE; LAURIC ISOPROPANOLAMIDE; SODIUM CARBONATE; GLYCOL DISTEARATE; .GAMMA.-DECALACTONE; METHYLISOTHIAZOLINONE; ETHYL METHYLPHENYLGLYCIDATE; CHLOROACETIC ACID; IONONE; BENZYL BENZOATE; MYRCENE; SODIUM HYDROXIDE; METHYL ANTHRANILATE; DIMETHYL BENZYL CARBINYL ACETATE; CALCIUM SILICATE; SODIUM LAURYL SULFATE; METHYLCHLOROISOTHIAZOLINONE; METHYL ALCOHOL; ETHYLENE OXIDE; LINALOOL, (+/-)-; DIOXANE; TRIBASIC CALCIUM PHOSPHATE; SODIUM ALUMINIUM SILICATE; WATER; SODIUM LAURETH SULFATE; COCAMIDOPROPYL BETAINE; PHENOXYETHANOL; COCO MONOISOPROPANOLAMIDE; PROPYLENE GLYCOL

Fastenal Antibacterial Skin Cleanser

Active Ingredient

Chloroxylenol 0.40%

Uses

- Antibacterial hand cleaner.
- Use in daycare, hospitals, nursing homes, physicians offices, dental offices and clinics

Warnings

- For external use only.
- Avoid contact with eyes.
- Children under the age of 6 should be supervised by an adult when using this product.
- Discontinue use is irritation or redness develops.
- If irritation persists for more than 72 hours, consult a physician.
- KEEP OUT OF REACH OF CHILDREN.
- If swallowed, get medical help or contact a Poison Control Center right away.

Directions

- Read the entire label before using this product.
- Dispense 2 pumps of product onto palm of hand and scrub thoroughly over all surfaces of both hands.
- Rinse with clean water.

Inactive Ingredients

Water, Sodium Laureth lSulfate, Cocamidopropyl betadine, Phenoxyethanol, Coco MIPA, Glycol Stearate, DMDM Hydantoin, Propylene Glycol, Sodium Chloride, Fragrance, Glycerin, Ethanol, D&C Green #5, FD&C Yellow #5.

Purpose

Antibacterial

KEEP OUT OF REACH OF CHILDREN

Winning Hands Antibacterial

KEEP OUT OF REACH OF CHILDREN

©2017 Betco Corporation
400 Van Camp Road Bowling Green, Ohio 43402
Made In U.S.A. All Rights Reserved.

888-GO BETCO (888-462-3826) | Betco.com